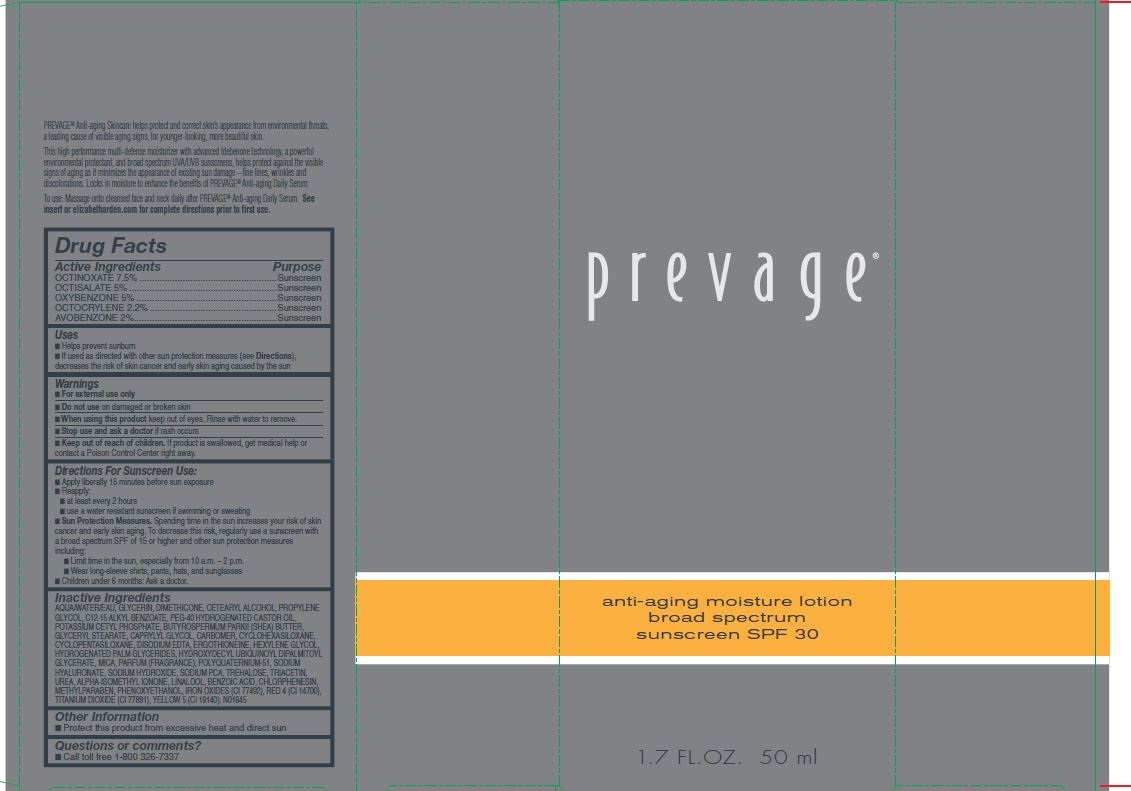 DRUG LABEL: Prevage anti aging SPF 30
NDC: 10967-686 | Form: LOTION
Manufacturer: Revlon
Category: otc | Type: HUMAN OTC DRUG LABEL
Date: 20251229

ACTIVE INGREDIENTS: OCTINOXATE 7.5 g/1 mL; OCTOCRYLENE 2.2 mg/1 mL; OCTISALATE 5 mg/1 mL; AVOBENZONE 2 mg/1 mL; OXYBENZONE 5 mg/1 mL
INACTIVE INGREDIENTS: MICA; TITANIUM DIOXIDE; CETOSTEARYL ALCOHOL; PROPYLENE GLYCOL; ALKYL (C12-15) BENZOATE; CARBOMER 1342; DIMETHICONE 1000; WATER; GLYCERIN; BUTYLATED HYDROXYTOLUENE; CHLORPHENESIN; METHYLPARABEN; FERRIC OXIDE RED; SODIUM PYRROLIDONE CARBOXYLATE; FERRIC OXIDE YELLOW; SHEA BUTTER; HYDROXYDECYL UBIQUINOYL DIPALMITOYL GLYCERATE; HYALURONATE SODIUM; TREHALOSE; HYDROGENATED PALM GLYCERIDES; POLYOXYL 40 HYDROGENATED CASTOR OIL; POLYQUATERNIUM-51 (2-METHACRYLOYLOXYETHYL PHOSPHORYLCHOLINE/N-BUTYL METHACRYLATE; 4:1); LINALOOL, (+/-)-; PHENOXYETHANOL; FD&C RED NO. 4; FD&C YELLOW NO. 5; POTASSIUM CETYL PHOSPHATE; ACRYLIC ACID; GLYCERYL STEARATE SE; SODIUM HYDROXIDE; CYCLOMETHICONE 5; CYCLOMETHICONE 6; ERGOTHIONEINE; UREA; ISOMETHYL-.ALPHA.-IONONE; 2-(4-(DIETHYLAMINO)-2-HYDROXYBENZOYL)BENZOIC ACID

Prevage Anti-aging moisture lotion SPF 30

ACTIVE INGREDIENTS

OCTINOXATE, 7.5 %

OCTISALATE, 5.0 %

OXYBENZONE, 5.0 %

OCTOCRYLENE, 2.2 %

AVOBENZONE, 2.0 %

Inactive Ingredients

WATER/AQUA/EAU, GLYCERIN, DIMETHICONE, CETEARYL ALCOHOL, PROPYLENE GLYCOL, C12-15 ALKYL BENZOATE, PEG-40 HYDROGENATED CASTOR OIL, POTASSIUM CETYL PHOSPHATE, GLYCERYL POLYACRYLATE, GLYCERYL STEARATE, BUTYROSPERMUM PARKII (SHEA) BUTTER, CARBOMER, CYCLOHEXASILOXANE, CYCLOPENTASILOXANE, ERGOTHIONEINE, HYDROGENATED PALM GLYCERIDES, HYDROXYDECYL UBIQUINOYL DIPALMITOYL GLYCERATE, MICA, PARFUM/FRAGRANCE, POLYQUATERNIUM-51, SODIUM HYALURONATE, SODIUM HYDROXIDE, SODIUM PCA, TREHALOSE, UREA, BHT, ALPHA-ISOMETHYL IONONE, LINALOOL, BENZOIC ACID, CHLORPHENESIN, METHYLPARABEN, PHENOXYETHANOL, IRON OXIDES, YELLOW (CI 77492), RED 4 (CI 14700), TITANIUM DIOXIDE (CI 77891), YELLOW 5 (CI 19140).

Purpose

Helps prevent sunburn

If used as directed with other sun protection measures (see Directions), decreases the risk of skin cancer and early skin aging caused by the sun.

Warnings

For external use only

Do not use on damaged or broken skin

When using this product keep out of eyes. Rinse with water to remove.

Stop using and ask a docotr is rash occurs.

Keep out of reach of children. if product is swallowed, get medical help or contact a Poison Control Center right away.

Directions For Sunscreen Use:

Apply liberally 15 minutes before sun exposure

Replly:

- at least every 2 hours

- use a water resistant sunscreen if swimming or sweating

Sun Protection measures. Spending time in the sun increases your risk od skin cancer and warly skin aging. To decrease this risk, regularly use a sunscreen with a broad spectrum SPF of 15 or higher and other sun protection measures including:

-Limit time in the sun, especially from 10 a.m. - 2 p.m.

-Wear long sleeve shirts, pants, hats and sunglasses.

- Children under 6 months: Ask a doctor.

INDICATIONS AND USAGE

- Helps prevent sunburn
- If used as directed with other sun protection measures (see Directions), decreases the risk of skin cancer and early skin againg caused by the sun